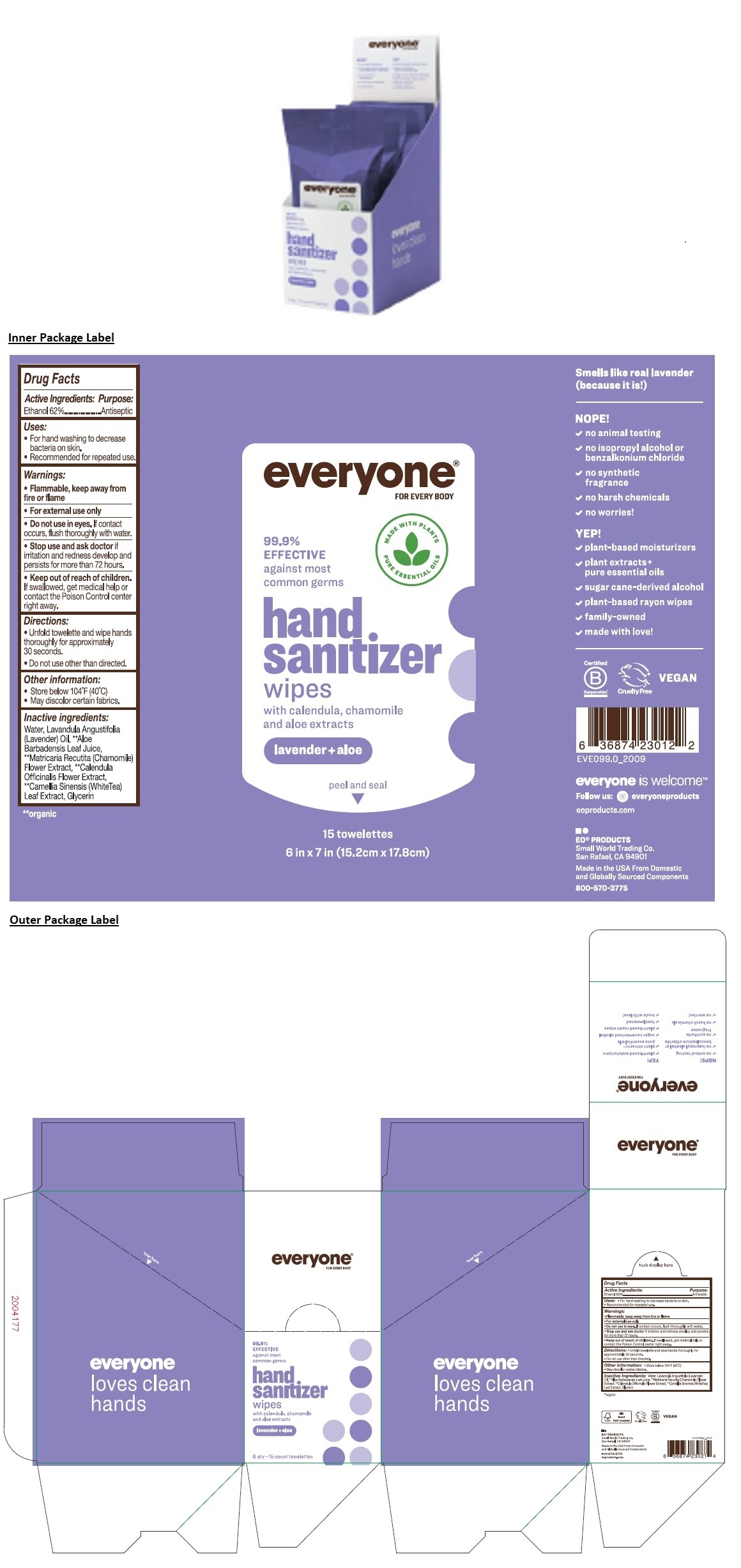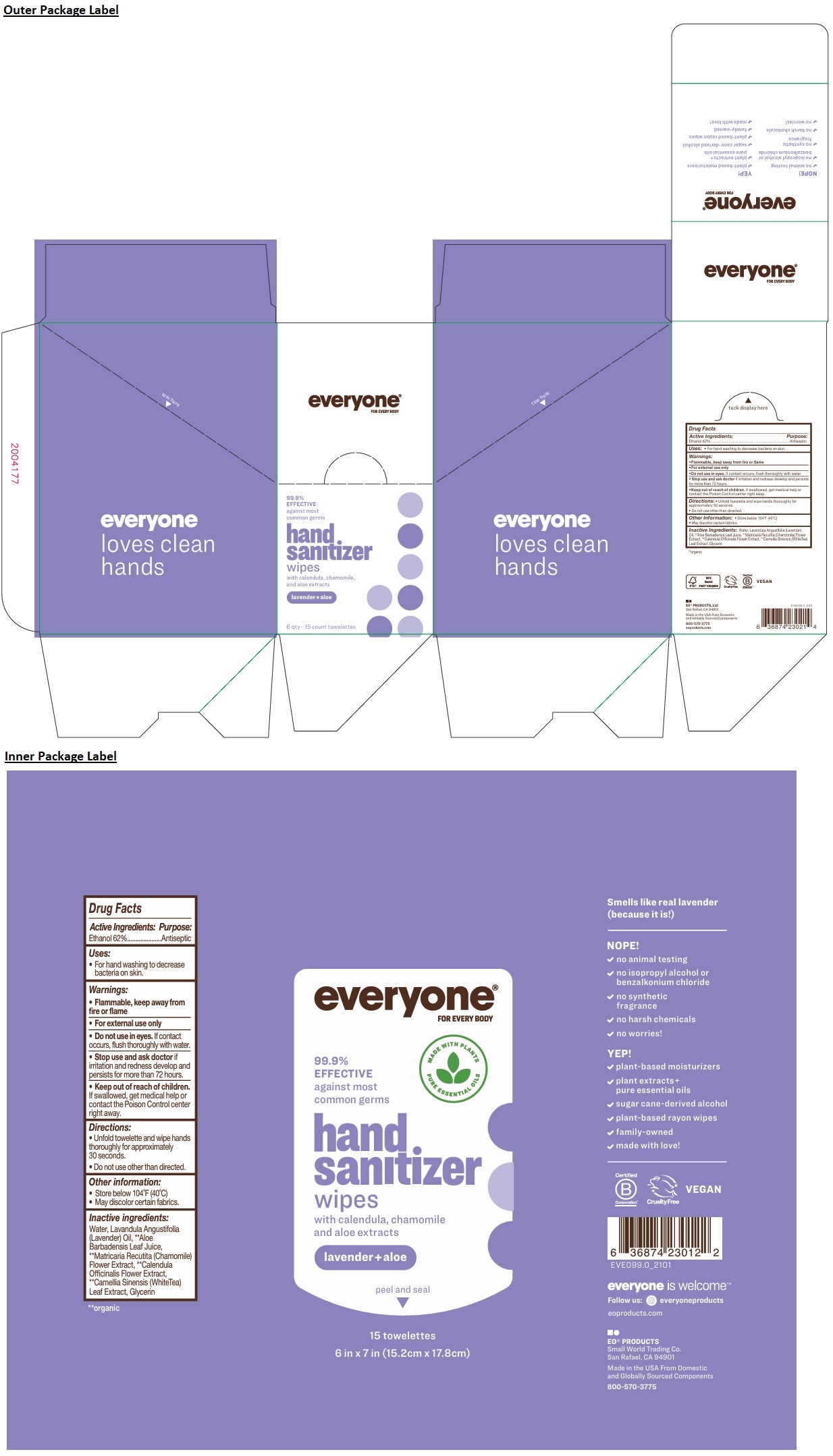 DRUG LABEL: everyone hand sanitizer wipes
NDC: 54748-702 | Form: CLOTH
Manufacturer: EO Products, LLC
Category: otc | Type: HUMAN OTC DRUG LABEL
Date: 20251120

ACTIVE INGREDIENTS: ALCOHOL 62 mL/100 mL
INACTIVE INGREDIENTS: WATER; LAVENDER OIL; ALOE VERA LEAF JUICE; CHAMOMILE; CALENDULA OFFICINALIS FLOWER; WHITE TEA; GLYCERIN

everyone® FOR EVERY BODY hand sanitizer wipes lavender + aloe

Active Ingredients:

Ethanol 62%

Purpose:

Antiseptic

Uses:

- For hand washing to decrease bacteria on skin.

Warnings:

- Flammable, keep away from fire or flame
- For external use only
- Do not use in eyes. If contact occurs, flush thoroughly with water.
- Stop use and ask doctor if irritation and redness develop and persists for more than 72 hours.

- Keep out of reach of children. If swallowed, get medical help or contact the Poison Control center right away.

Directions:

- Unfold towelette and wipe hands thoroughly for approximately 30 seconds.
- Do not use other than directed.

Other Information:

- Store below 104°F (40°C)
- May discolor certain fabrics.

Inactive Ingredients:

Water, Lavandula Angustifolia (Lavender) Oil, **Aloe Barbadensis Leaf Juice, **Matricaria Recutita (Chamomile) Flower Extract, **Calendula Officinalis Flower Extract, **Camellia Sinensis (White Tea) Leaf Extract, Glycerin

**organic

99.9% EFFECTIVE against most common germs

with calendula, chamomile, and aloe extracts

everyone loves clean hands

Cruelty Free

VEGAN

EO® PRODUCTS, LLC
Small World Trading Co.
San Rafael, CA 94901

Made in the USA From Domestic and Globally Sourced Components

800-570-3775
eoproducts.com

NOPE!

✓ no animal testing

✓ no isopropyl alcohol or benzalkonium chloride

✓ no synthetic fragrance

✓ no harsh chemicals

✓ no worries!

YEP!

✓ plant-based moisturizers

✓ plant extracts + pure essential oils

✓ sugar cane-derived alcohol

✓ plant-based rayon wipes

✓ family-owned

✓ made with love!

MADE WITH PLANTS PURE ESSENTIAL OILS

Smells like real lavender
(because it is!)

everyone is welcome™

Follow us: everyoneproducts

eoproducts.com